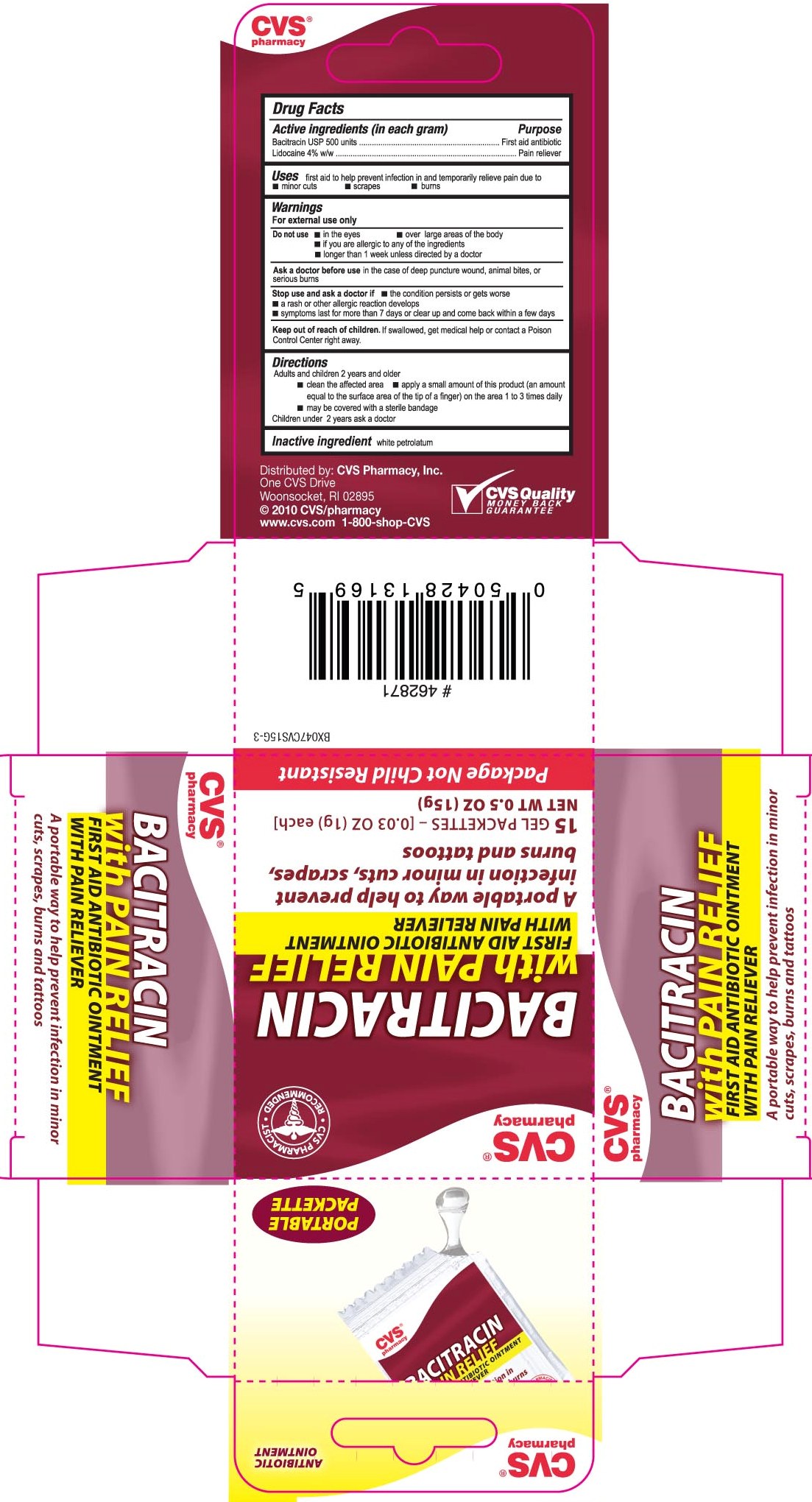 DRUG LABEL: CVS Bacitracin with Pain Relief
NDC: 59779-537 | Form: OINTMENT
Manufacturer: CVS Pharmacy
Category: otc | Type: HUMAN OTC DRUG LABEL
Date: 20110802

ACTIVE INGREDIENTS: BACITRACIN 600 [USP'U]/1 g; LIDOCAINE 40 mg/1 g
INACTIVE INGREDIENTS: PETROLATUM

DRUG FACTS

Active ingredient Purpose
Bacitracin, USP 500 units..................................................First Aid Antibiotic
Lidocaine 4% w/w..............................................................Pain Reliever

Uses
- first aid to help prevent infection in and temporarily relieve pain due to
- minor cuts - scrapes - burns

Keep out of reach of children. If swallowed, get medical help or contact a
Poison Control Center right away.

Uses
- first aid to help prevent infection in and temporarily relieve pain due to
- minor cuts - scrapes - burns

Warnings
For external use only
Do not use - in the eyes - over large areas of the body
- if you are allergic to any of the ingredients
- longer than 1 week unless directed by a doctor
Ask a doctor before use in the case of a deep puncture wound, animal bites or serious burns
Stop use and ask a doctor if - the condition persists or gets worse
- a rash or other allergic reaction develops
- symptoms last for more than 7 days or clear up and come back within a few days
Keep out of reach of children. If swallowed, get medical help or contact a
Poison Control Center right away.

Directions
Adults and children 2 years and older
- clean the affected area - apply a small amount of this product (an amount equal
to the surface area of the tip of a finger) on the area 1 to 3 times daily
- may be covered with a sterile bandage
Children under 2 years ask a doctor

Inactive Ingredients
white petrolatum